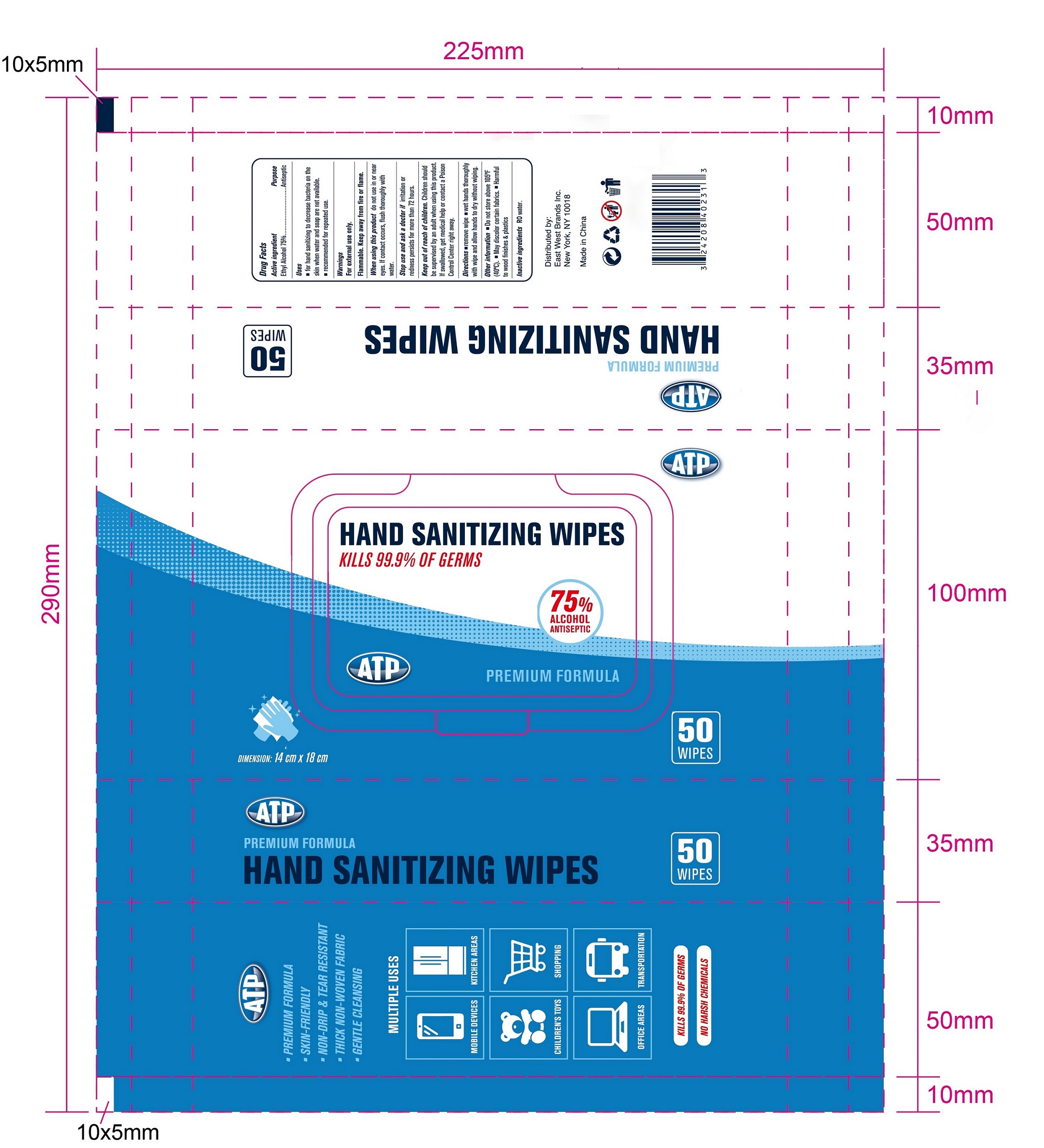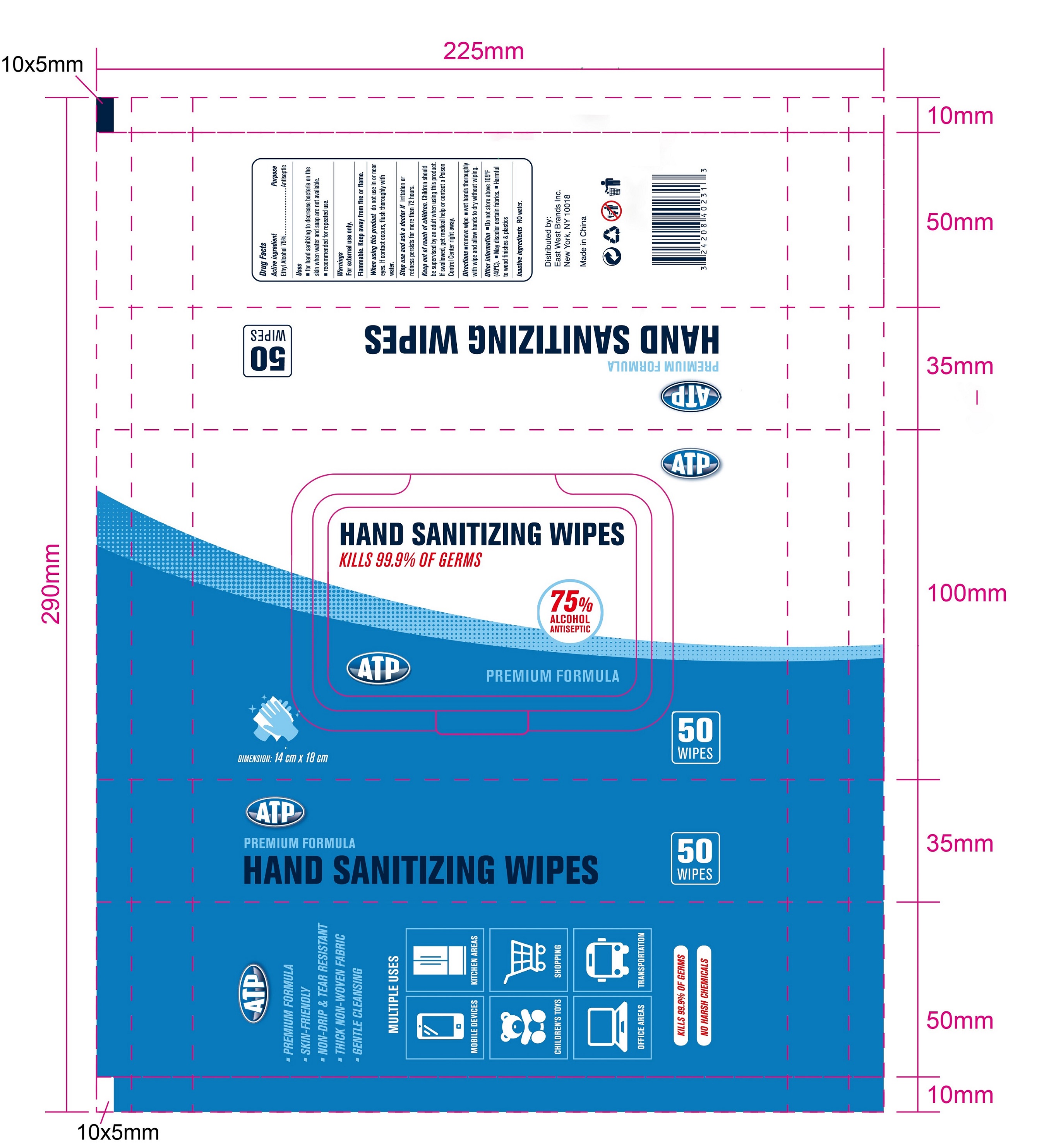 DRUG LABEL: ALCOHOL WIPES
NDC: 73960-006 | Form: CLOTH
Manufacturer: EAST WEST BRANDS INC.
Category: otc | Type: HUMAN OTC DRUG LABEL
Date: 20200619

ACTIVE INGREDIENTS: ALCOHOL 3.5 mL/1 1
INACTIVE INGREDIENTS: WATER

73960-006

Active Ingredient(s)

Alcohol 75% v/v. Purpose: Antiseptic

Inactive ingredients

Water

Purpose

Daily Clean for daily items and Antimicrobial.

WHEN USING

This product is used to wipe hands, faces, skins, etc. It can also be used to clean many kinds of places.

Do not use

on children less than 2 months of age
on open skin wounds

STOP USE

if irritation or rash occurs.

These may be signs of a serious condition.

Keep out of reach of children.

Use

This product is used to wipe hands, faces, skins, etc. It can also be used to clean many kinds of places.

Open the label, take out the wet towel and wipe the target area.

Directions

Use it as needed, after following the usage instructions.

For external use only.

Warnings

Do not apply this product to red and swollen skin, wound or any part sensitive to it.

Keep this product out of children’s reach in case they might eat it.
Alcohol is violatile, please use it as soon as possible after opening, store it in a cool and dry place, avoid direct sunlight and open fire, and avoid contact with eyes and damaged skin.

Other information

- Store between 15-30C (59-86F)
- Avoid freezing and excessive heat above 40C (104F)

Package Label - Principal Display Panel

50 CLOTH IN 1 BAG NDC:73960-006-01